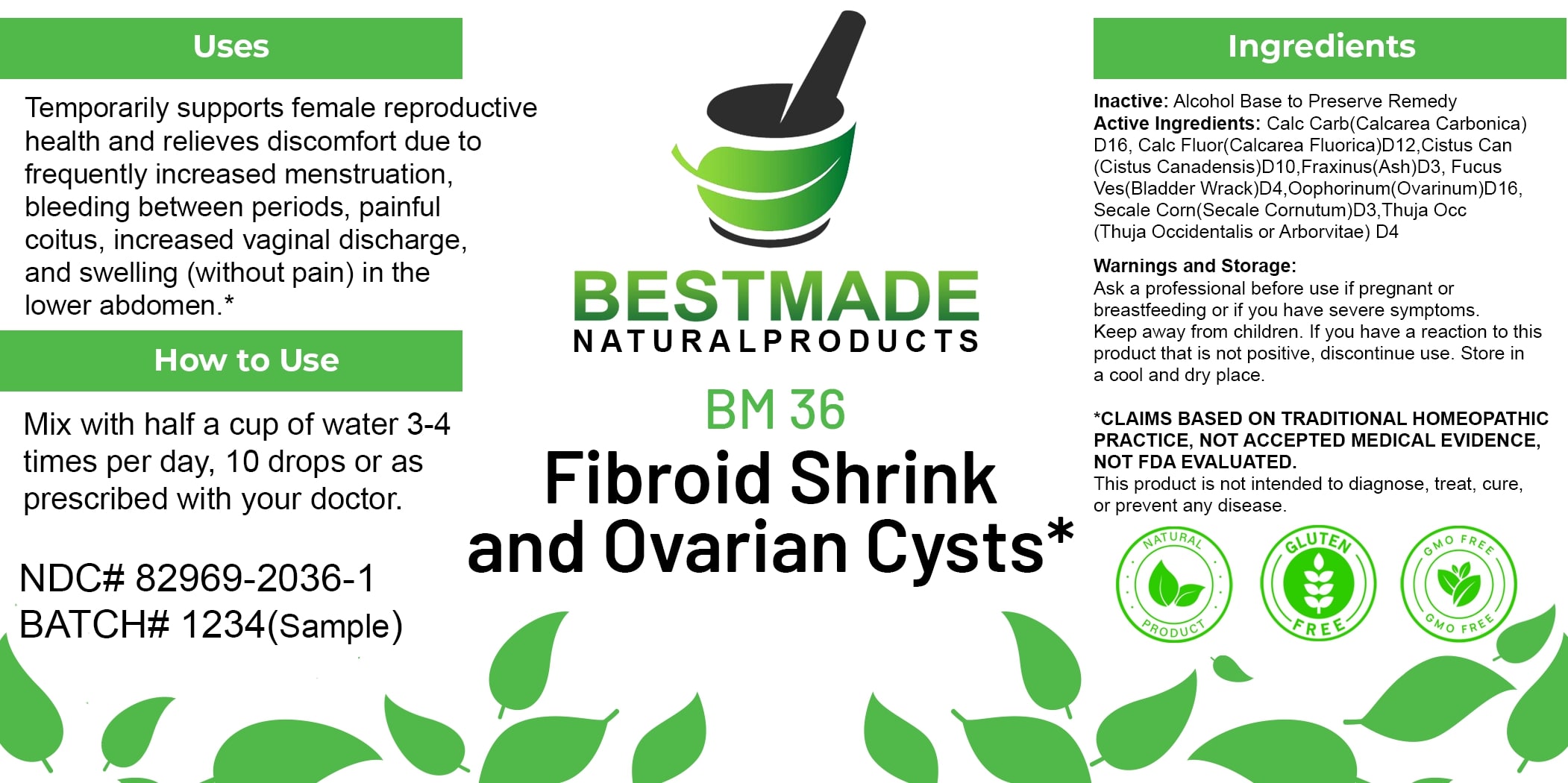 DRUG LABEL: Bestmade Natural Products BM36
NDC: 82969-2036 | Form: LIQUID
Manufacturer: Bestmade Natural Products
Category: homeopathic | Type: HUMAN OTC DRUG LABEL
Date: 20250123

ACTIVE INGREDIENTS: HELIANTHEMUM CANADENSE 30 [hp_C]/30 [hp_C]; THUJA OCCIDENTALIS LEAF 30 [hp_C]/30 [hp_C]; CLAVICEPS PURPUREA SCLEROTIUM 30 [hp_C]/30 [hp_C]; CALCIUM CARBONATE 30 [hp_C]/30 [hp_C]; CALCIUM FLUORIDE 30 [hp_C]/30 [hp_C]; FRAXINUS AMERICANA POLLEN 30 [hp_C]/30 [hp_C]; FUCUS VESICULOSUS 30 [hp_C]/30 [hp_C]
INACTIVE INGREDIENTS: ALCOHOL 30 [hp_C]/30 [hp_C]

BM36

DOSAGE AND ADMINISTRATION

How to Use

Mix with half a cup of water 3-4 times per day, 10 drops or as prescribed with your doctor.

Uses

Temporarily supports female reproductive health and relieves discomfort due to frequently increased menstruation, bleeding between periods, painful coitus, increased vaginal discharge, and swelling (without pain) in the lower abdomen.*

*CLAIMS BASED ON TRADITIONAL HOMEOPATHIC PRACTICE, NOT ACCEPTED MEDICAL EVIDENCE, NOT FDA EVALUATED.

This product is not intended to diagnose, treat, cure, or prevent any disease.

Uses

Temporarily supports female reproductive health and relieves discomfort due to frequently increased menstruation, bleeding between periods, painful coitus, increased vaginal discharge, and swelling (without pain) in the lower abdomen.*

*CLAIMS BASED ON TRADITIONAL HOMEOPATHIC PRACTICE, NOT ACCEPTED MEDICAL EVIDENCE, NOT FDA EVALUATED.

This product is not intended to diagnose, treat, cure, or prevent any disease.

ACTIVE INGREDIENT

Active Ingredients: Calc Carb (Calcarea Carbonica) D16, Calc Fluor (Calcarea Fluorica) D12, Cistus Can (Cistus Canadensis) D10, Fraxinus (Ash) D3, Fucus Ves (Bladder Wrack) D4, Oophorinum (Ovarinum) D16, Secale Corn (Secale Cornutum) D3, Thuja Occ (Thuja Occidentalis or Arborvitae) D4

INACTIVE INGREDIENT

Ingredients

Inactive: Alcohol Base to Preserve Remedy

KEEP OUT OF REACH OF CHILDREN

Warnings and Storage:

Ask a professional before use if pregnant or breastfeeding or if you have severe symptoms. Keep away from children. If you have a reaction to this product that is not positive, discontinue use. Store in a cool and dry place.

Warnings and Storage:

Ask a professional before use if pregnant or breastfeeding or if you have severe symptoms. Keep away from children. If you have a reaction to this product that is not positive, discontinue use. Store in a cool and dry place.

*CLAIMS BASED ON TRADITIONAL HOMEOPATHIC PRACTICE, NOT ACCEPTED MEDICAL EVIDENCE, NOT FDA EVALUATED.

This product is not intended to diagnose, treat, cure, or prevent any disease.

Entire package label